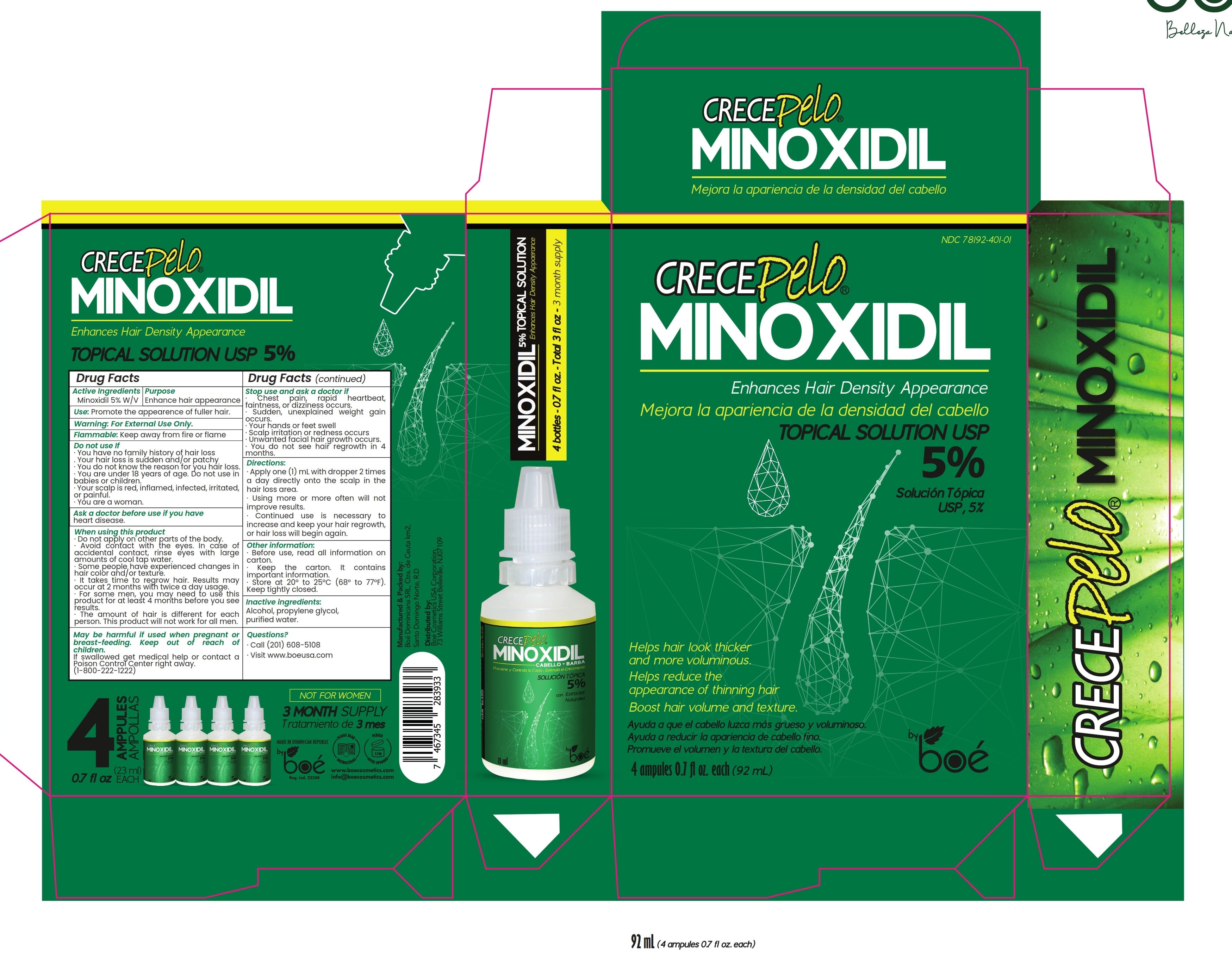 DRUG LABEL: SOLUCION CAPILAR CRECEPELO
NDC: 78192-401 | Form: LIQUID
Manufacturer: BOE Dominicana SRL
Category: otc | Type: HUMAN OTC DRUG LABEL
Date: 20250128

ACTIVE INGREDIENTS: MINOXIDIL 5 mg/30 mL
INACTIVE INGREDIENTS: PROPYLENE GLYCOL; ALCOHOL; WATER 1 mL/30 mL

Boe Minoxidil

Active ingredients

MINOXIDIL 5%

Purpose

Active ingredients | Purpose
Minoxidil 5% W/V | Enhance hair appearance

Use: Promote the appearence of fuller hair.

WARNINGS

For External Use Only

Flammable: Keep away from fire or flame

Do not use if

- You have no family history of hair loss .
- Your hair loss is sudden and/or patchy ·
- You do not know the reason for you hair loss. ·
- You are under 18 years of age.
- Do not use in babies or children. ·
- Your scalp is red, inflamed, infected, irritated, or painful.

Ask a doctor before use if you have

heart disease

When using this product

- Do not apply on other parts of the body.
- Avoid contact with the eyes. In case of accidental contact, rinse eyes with large amounts of cool tap water.
- Some people have experienced changes in hair color and/or texture. ·
- It takes time to regrow hair. Results may occur at 2 months with twice a day usage.
- For some men, you may need to use this product for at least 4 months before you see results.
- The amount of hair is different for each person. This product will not work for all men.

Pregnancy section

May be harmful if used when pregnant or breast-feeding.

Keep out of reach of children.

If swallowed get medical help or contact a Poison Control Center right away. (1-800-222-1222)

Stop use and ask a doctor if

- Chest pain, rapid heartbeat, faintness, or dizziness occurs. ·
- Sudden, unexplained weight gain occurs. ·
- Your hands or feet swell ·
- Scalp irritation or redness occurs ·
- Unwanted facial hair growth occurs.
- You do not see hair regrowth in 4 months.

Other information

- Before use, read all information on carton.
- Keep the carton. It contains important information.
- Store at 20° to 25°C (68° to 77°F). Keep tightly closed.

Directions

- Apply one (1) mL with dropper 2 times a day directly onto the scalp in the hair loss area.
- Using more or more often will not improve results.
- Continued use is necessary to increase and keep your hair regrowth, or hair loss will begin again

INDICATIONS AND USAGE

use as directed

INACTIVE INGREDIENT

Alcohol, propylene glycol, purified water.

Questions?

- Call (201) 608-5108
- Visit www.boeusa.com

PACKAGE LABEL

NDC 78192-400-01

CRECEPELO®

MINOXIDIL

Enhances Hair Density Appearance

Mejora la apariencia de la densidad del cabello

TOPICAL SOLUTION USP 5%

Solución tópica USP, 5%

Helps hair look thicker and more voluminous.

Helps reduce the appearance of thinning hair

Boost hair volume and texture

Ayuda a que el cabello luzca más grueso y voluminoso. Ayuda a reducir la apariencia de cabello fino. Promueve el volumen y la textura del cabello

NOT FOR WOMEN

3 MONTH SUPPLY

Tratamiento de 3 mes

4 ampules 0.7 fl oz. each (92 mL)

Manufactured & Packed by: Boé Dominicana SRL, Ctra. de Ceuta km2, Santo Domingo Norte, RD

Distributed by: Boé Cosmetics USA Corporation, 73 Williams Street Belleville, NJ07109